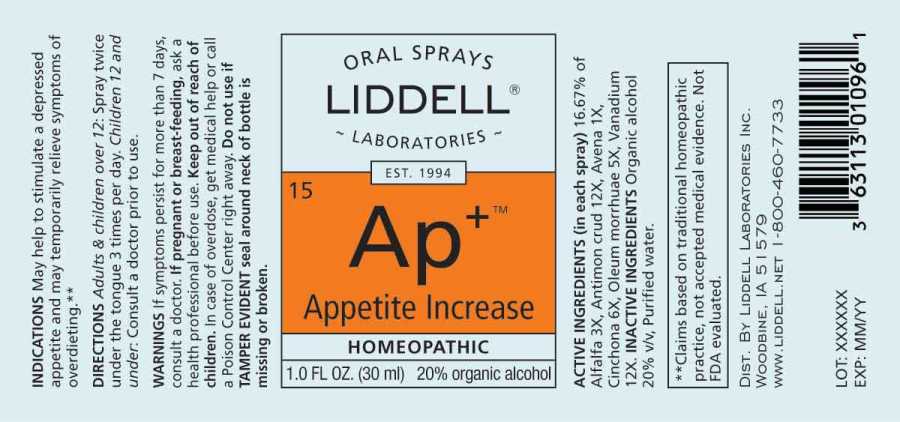 DRUG LABEL: Appetite Increase
NDC: 50845-0279 | Form: SPRAY
Manufacturer: Liddell Laboratories, Inc.
Category: homeopathic | Type: HUMAN OTC DRUG LABEL
Date: 20241104

ACTIVE INGREDIENTS: MEDICAGO SATIVA WHOLE 3 [hp_X]/1 mL; ANTIMONY TRISULFIDE 12 [hp_X]/1 mL; AVENA SATIVA FLOWERING TOP 1 [hp_X]/1 mL; CINCHONA OFFICINALIS BARK 6 [hp_X]/1 mL; COD LIVER OIL 5 [hp_X]/1 mL; VANADIUM 12 [hp_X]/1 mL
INACTIVE INGREDIENTS: WATER; ALCOHOL

DRUG FACTS:

ACTIVE INGREDIENTS:

(in each spray) 16.67% of Alfalfa 3X, Antimonium Crudum 12X, Avena Sativa 1X, Cinchona Officinalis 6X, Oleum Morrhuae 5X, Vanadium Metallicum 12X.

INDICATIONS:

May help to stimulate a depressed appetite and may temporarily relieve symptoms of overdieting.**

**Claims based on traditional homeopathic practice, not accepted medical evidence. Not FDA evaluated.

WARNINGS:

If symptoms persist for more than 7 days, consult a doctor.

If pregnant or breast feeding, ask a health professional before use.

Keep out of reach of children. In case of overdose, get medical help or call a Poison Control Center right away.

Do not use if TAMPER EVIDENT seal around neck of bottle is missing or broken.

Keep out of reach of children. In case of overdose, get medical help or call a Poison Control Center right away.

DIRECTIONS:

Adults and children over 12: Spray twice under the tongue 3 times per day.

Children 12 and under: Consult a doctor prior to use.

INDICATIONS:

May help to stimulate a depressed appetite and may temporarily relieve symptoms of overdieting.**

**Claims based on traditional homeopathic practice, not accepted medical evidence. Not FDA evaluated.

INACTIVE INGREDIENTS:

Organic alcohol 20% v/v, Purified water.

QUESTONS:

DIST. BY LIDDELL LABORATORIES INC.

WOODBINE, IA 51579

WWW.LIDDELL.NET 1-800-460-7733

PACKAGE LABEL DISPLAY:

ORAL SPRAYS

LIDDELL

LABORATORIES

15 Ap+

Appetite Increase

HOMEOPATHIC

1.0 FL OZ. (30 ml)